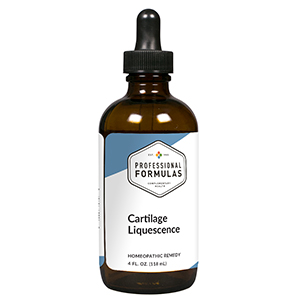 DRUG LABEL: Cartilage Liquescence
NDC: 63083-3020 | Form: LIQUID
Manufacturer: Professional Complementary Health Formulas
Category: homeopathic | Type: HUMAN OTC DRUG LABEL
Date: 20190815

ACTIVE INGREDIENTS: SAW PALMETTO 1 [hp_X]/118 mL; STRYCHNOS WALLICHIANA WHOLE 3 [hp_X]/118 mL; ARNICA MONTANA WHOLE 3 [hp_X]/118 mL; BOVINE TYPE II COLLAGEN (TRACHEAL CARTILAGE) 3 [hp_X]/118 mL; SHARK CARTILAGE 3 [hp_X]/118 mL; THUJA OCCIDENTALIS LEAF 3 [hp_X]/118 mL; APIS MELLIFERA 6 [hp_X]/118 mL; ARSENIC TRIBROMIDE 6 [hp_X]/118 mL; THYMOL 6 [hp_X]/118 mL; HYSSOPUS OFFICINALIS WHOLE 6 [hp_X]/118 mL; ARSENIC TRIIODIDE 12 [hp_X]/118 mL
INACTIVE INGREDIENTS: ALCOHOL; WATER

T20

ACTIVE INGREDIENTS

Sabal serrulata 1X, 3X
Hoang nan 3X
Arnica montana 3X, 6X, 30X
Cartilage (bovine) 3X, 6X, 30X, 60X, 100X
Cartilage (shark) 3X, 6X, 30X, 60X, 100X
Thuja occidentalis 3X, 6X, 30X
Apis mellifica 6X
Arsenicum bromatum 6X
Thymolum 6X
Thymus 6X, 30X
Arsenicum iodatum 12X, 30X, 100X

QUESTIONS

Professional Formulas

PO Box 2034 Lake Oswego, OR 97035

INDICATIONS

For the temporary relief of mild joint or muscle inflammation, stiffness, pain, or tenderness, general weakness, or fatigue.*

PURPOSE

*Claims based on traditional homeopathic practice, not accepted medical evidence. Not FDA evaluated.

WARNINGS

In case of overdose, get medical help or contact a poison control center right away.

Keep out of the reach of children.

PREGNANCY OR BREAST FEEDING

If pregnant or breastfeeding, ask a healthcare professional before use.

DIRECTIONS

Place drops under tongue 30 minutes before/after meals. Adults and children 12 years and over: Take one full dropper up to 2 times per day. Consult a physician for use in children under 12 years of age.

OTHER INFORMATION

Tamper resistant. If seal is broken, do not use. After opening, close container tightly and store at room temperature away from heat.

INACTIVE INGREDIENTS

20% ethanol, purified water.

LABEL

Est 1985

Professional Formulas

Complementary Health

Cartilage Liquescence

Homeopathic Remedy

4 FL. OZ. (118 mL)